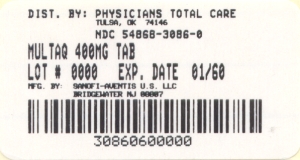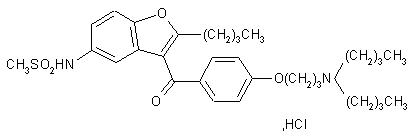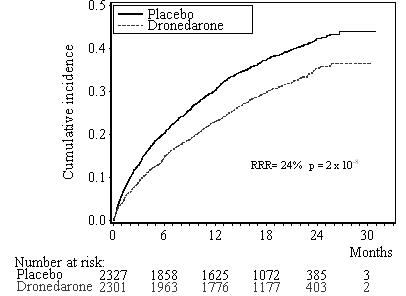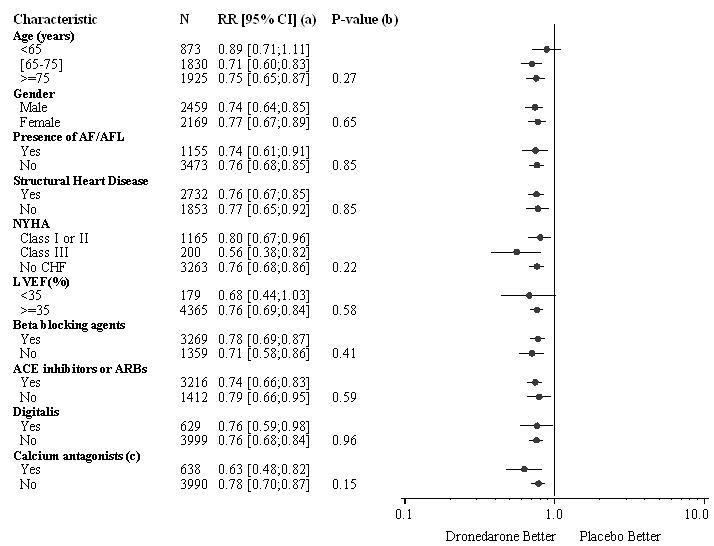 DRUG LABEL: Multaq
NDC: 54868-3086 | Form: TABLET, FILM COATED
Manufacturer: Physicians Total Care, Inc.
Category: prescription | Type: HUMAN PRESCRIPTION DRUG LABEL
Date: 20111228

ACTIVE INGREDIENTS: Dronedarone 400 mg/1 1
INACTIVE INGREDIENTS: hypromelloses; starch, corn; crospovidone; poloxamer 407; lactose monohydrate; silicon dioxide; magnesium stearate; polyethylene glycol 6000; titanium dioxide; carnauba wax

HIGHLIGHTS OF PRESCRIBING INFORMATION

These highlights do not include all the information needed to use MULTAQ safely and effectively. See full prescribing information for MULTAQ.
MULTAQ (dronedarone) Tablets
Initial U.S. Approval: 2009

WARNING: INCREASED RISK OF DEATH, STROKE AND HEART FAILURE IN PATIENTS WITH DECOMPENSATED HEART FAILURE OR PERMANENT ATRIAL FIBRILLATION

MULTAQ is contraindicated in patients with symptomatic heart failure with recent decompensation requiring hospitalization or NYHA Class IV heart failure. MULTAQ doubles the risk of death in these patients (4, 5.1, 14.3).

MULTAQ is contraindicated in patients in atrial fibrillation (AF) who will not or cannot be cardioverted into normal sinus rhythm. In patients with permanent AF, MULTAQ doubles the risk of death, stroke, and hospitalization for heart failure. (4, 5.2,14.4)

RECENT MAJOR CHANGES

• Warnings and Precautions, Liver Injury (5.5) | 02/2011
• Warnings and Precautions, Increase in Creatinine after Treatment Initiation (5.8) | 08/2011
• Indications and Usage, (1), Contraindications (4), Warnings and Precautions (5.1, 5.2, 5.3, 5.4) 5.5) | xx/2011

1 INDICATIONS AND USAGE

MULTAQ is an antiarrhythmic drug indicated to reduce the risk of hospitalization for atrial fibrillation (AF) in patients in sinus rhythm with a history of paroxysmal or persistent AF (1, 14).

2 DOSAGE AND ADMINISTRATION

One tablet of 400 mg twice a day with morning and evening meals (2)

3 DOSAGE FORMS AND STRENGTHS

400 mg film-coated tablets (3)

4 CONTRAINDICATIONS

- Permanent AF (patients in whom normal sinus rhythm will not or cannot be restored) (Boxed Warning, 4)
- Recently decompensated heart failure requiring hospitalization or Class IV heart failure. (Boxed Warning, 4)
- Second- or third- degree atrioventicular (AV) block or sick sinus syndrome (except when used in conjunction with a functioning pacemaker) (4)
- Bradycardia <50 bpm (4)
- Concomitant use of a strong CYP3A inhibitor (4)
- Concomitant use of drugs or herbal products that prolong the QT interval and may induce Torsade de Pointes (4)
- Liver toxicity related to the previous use of amiodarone (4)
- Severe hepatic impairment (4)
- QTc Bazett interval ≥500 ms (4)
- Pregnancy (4, 8.1) and Nursing mothers (4, 8.3)

5 WARNINGS AND PRECAUTIONS

- Determine cardiac rhythm at least once every 3 months. If AF is detected discontinue MULTAQ or cardiovert (5.2).
- Liver injury: if hepatic injury is suspected, discontinue MULTAQ (5.5)
- Ensure appropriate antithrombotic therapy prior to and throughout MULTAQ use. (5.3)
- Hypokalemia and hypomagnesemia: Maintain potassium and magnesium levels within the normal range (5.6)
- Increase in creatinine: Monitor serum creatinine periodically (5.8)
- 5)
- Teratogen: Women of childbearing potential should use effective contraception while using MULTAQ (5.9)

6 ADVERSE REACTIONS

Most common adverse reactions (≥2%) are diarrhea, nausea, abdominal pain, vomiting, and asthenia (6)

To report SUSPECTED ADVERSE REACTIONS, contact sanofi-aventis U.S. LLC at 1-800-633-1610 or FDA at 1-800-FDA-1088 or www.fda.gov/medwatch

7 DRUG INTERACTIONS

Dronedarone is metabolized by CYP 3A and is a moderate inhibitor of

CYP 3A and CYP 2D6 and has potentially important pharmacodynamic interactions (7)

- Antiarrhythmics: Avoid concomitant use (4, 7.1)
- Digoxin: Consider discontinuation or halve dose of digoxin before treatment and monitor digoxin levels (7.1, 7.3)
- Calcium channel blockers (CCB): Initiate CCB with low dose and increase after ECG verification of tolerability (7.1,7.2, 7.3)
- Beta-blockers: May provoke excessive bradycardia, Initiate with low dose and increase after ECG verification of tolerability (7.1, 7.3)
- CYP 3A inducers: Avoid concomitant use (7.2)
- Grapefruit juice: Avoid concomitant use (7.2)
- Statins: Follow label recommendations for concomitant use of certain statins with a CYP 3A and P-gP inhibitor like dronedarone (7.3)
- CYP 3A substrates with a narrow therapeutic index (e.g., sirolimus and tacrolimus): Monitor and adjust dosage of concomitant drug as needed when used with MULTAQ (7.3)
- Warfarin: Monitor INR after initiating dronedarone in patients taking warfarin. (7.3)

FULL PRESCRIBING INFORMATION

WARNING: INCREASED RISK OF DEATH, STROKE AND HEART FAILURE IN PATIENTS WITH DECOMPENSATED HEART FAILURE OR PERMANENT ATRIAL FIBRILLATION

In patients with symptomatic heart failure and recent decompensation requiring hospitalization or NYHA Class IV heart failure; MULTAQ doubles the risk of death. (14.3) MULTAQ is contraindicated in patients with symptomatic heart failure with recent decompensation requiring hospitalization or NYHA Class IV heart failure. (4, 5.1)

In patients with permanent atrial fibrillation, MULTAQ doubles the risk of death, stroke and hospitalization for heart failure. (14.4). MULTAQ is contraindicated in patients in atrial fibrillation (AF) who will not or cannot be cardioverted into normal sinus rhythm. (4, 5.2)

1 INDICATIONS AND USAGE

MULTAQ® is indicated to reduce the risk of hospitalization for atrial fibrillation in patients in sinus rhythm with a history of paroxysmal or persistent atrial fibrillation (AF) [see Clinical Studies (14)].

2 DOSAGE AND ADMINISTRATION

The recommended dosage of MULTAQ is 400 mg twice daily in adults. MULTAQ should be taken as one tablet with the morning meal and one tablet with the evening meal.

Treatment with Class I or III antiarrhythmics (e.g., amiodarone, flecainide, propafenone, quinidine, disopyramide, dofetilide, sotalol) or drugs that are strong inhibitors of CYP3A (e.g., ketoconazole) must be stopped before starting MULTAQ [see Contraindications (4)].

3 DOSAGE FORMS AND STRENGTHS

MULTAQ 400 mg tablets are provided as white film-coated tablets for oral administration, oblong-shaped, engraved with a double wave marking on one side and "4142" code on the other side.

4 CONTRAINDICATIONS

MULTAQ is contraindicated in patients with:

- Permanent atrial fibrillation (patients in whom normal sinus rhythm will not or cannot be restored) [see Boxed Warning and Warnings and Precautions (5.2)]
- Symptomatic heart failure with recent decompensation requiring hospitalization or NYHA Class IV symptoms [see Boxed Warning and Warnings and Precautions (5.1)]
- Second- or third-degree atrioventricular (AV) block, or sick sinus syndrome (except when used in conjunction with a functioning pacemaker)
- Bradycardia <50 bpm
- Concomitant use of strong CYP 3A inhibitors, such as ketoconazole, itraconazole, voriconazole, cyclosporine, telithromycin, clarithromycin, nefazodone, and ritonavir [see Drug Interactions (7.2)]
- Concomitant use of drugs or herbal products that prolong the QT interval and might increase the risk of Torsade de Pointes, such as phenothiazine anti-psychotics, tricyclic antidepressants, certain oral macrolide antibiotics, and Class I and III antiarrhythmics
- Liver toxicity related to the previous use of amiodarone
- QTc Bazett interval ≥500 ms or PR interval >280 ms
- Severe hepatic impairment
- Pregnancy (Category X): MULTAQ may cause fetal harm when administered to a pregnant woman. MULTAQ is contraindicated in women who are or may become pregnant. If this drug is used during pregnancy, or if the patient becomes pregnant while taking this drug, the patient should be apprised of the potential hazard to a fetus [see Use in Specific Populations (8.1)].
- Nursing mothers [see Use in Specific Populations (8.3)]

5 WARNINGS AND PRECAUTIONS

5.1 Cardiovascular Death in NYHA Class IV or Decompensated Heart Failure

MULTAQ is contraindicated in patients with NYHA Class IV heart failure or symptomatic heart failure with recent decompensation requiring hospitalization because it doubles the risk of death.

5.2 Cardiovascular Death and Heart Failure in Permanent AF

MULTAQ doubles the risk of cardiovascular death (largely arrhythmic) and heart failure events in patients with permanent AF. Patients treated with dronedarone should undergo monitoring of cardiac rhythm no less often than every 3 months. Cardiovert patients who are in atrial fibrillation (if clinically indicated) or discontinue MULTAQ. MULTAQ offers no benefit in subjects in permanent AF.

5.3 Increased Risk of Stroke in Permanent AF

In a placebo-controlled study in patients with permanent atrial fibrillation, dronedarone was associated with an increased risk of stroke, particularly in the first two weeks of therapy [see Clinical Studies (14.4)]. MULTAQ should only be initiated in patients in sinus rhythm who are receiving appropriate antithrombotic therapy [see Drug interactions (7.3)].

5.4 New Onset or Worsening Heart Failure

New onset or worsening of heart failure has been reported during treatment with MULTAQ in the postmarketing setting. In a placebo controlled study in patients with permanent AF increased rates of heart failure were observed in patients with normal left ventricular function and no history of symptomatic heart failure, as well as those with a history of heart failure or left ventricular dysfunction.

Advise patients to consult a physician if they develop signs or symptoms of heart failure, such as weight gain, dependent edema, or increasing shortness of breath. If heart failure develops or worsens and requires hospitalization, discontinue MULTAQ.

5.5 Liver Injury

Hepatocellular liver injury, including acute liver failure requiring transplant, has been reported in patients treated with MULTAQ in the post-marketing setting. Advise patients treated with MULTAQ to report immediately symptoms suggesting hepatic injury (such as anorexia, nausea, vomiting, fever, malaise, fatigue, right upper quadrant pain, jaundice, dark urine, or itching). Consider obtaining periodic hepatic serum enzymes, especially during the first 6 months of treatment, but it is not known whether routine periodic monitoring of serum enzymes will prevent the development of severe liver injury. If hepatic injury is suspected, promptly discontinue MULTAQ and test serum enzymes, aspartate aminotransferase (AST), alanine aminotransferase (ALT) and alkaline phosphatase, as well as serum bilirubin, to establish whether there is liver injury. If liver injury is found, institute appropriate treatment and investigate the probable cause. Do not restart MULTAQ in patients without another explanation for the observed liver injury.

5.6 Hypokalemia and Hypomagnesemia with Potassium-Depleting Diuretics

Hypokalemia or hypomagnesemia may occur with concomitant administration of potassium-depleting diuretics. Potassium levels should be within the normal range prior to administration of MULTAQ and maintained in the normal range during administration of MULTAQ.

5.7 QT Interval Prolongation

Dronedarone induces a moderate (average of about 10 ms but much greater effects have been observed) QTc (Bazett) prolongation [see Clinical Pharmacology (12.2) and Clinical Studies (14.1)]. If the QTc Bazett interval is ≥500 ms, discontinue MULTAQ [see Contraindications (4)].

5.8 Increase in Creatinine after Treatment Initiation

Small increases in creatinine levels (about 0.1 mg/dL) following dronedarone treatment initiation have been shown to be a result of inhibition of creatinine's tubular secretion. ..

The elevation has a rapid onset, reaches a plateau after 7 days and is reversible after discontinuation.

Larger increases in creatinine after dronedarone initiation have been reported in the postmarketing setting. Some cases also reported increases in blood urea nitrogen. In most cases, these effects appear to be reversible upon drug discontinuation. Monitor renal function periodically.

5.9 Women of Childbearing Potential

Premenopausal women who have not undergone a hysterectomy or oophorectomy must use effective contraception while using MULTAQ. Dronedarone caused fetal harm in animal studies at doses equivalent to recommended human doses. Counsel women of childbearing potential regarding appropriate contraceptive choices. [see Use in Specific Populations (8.1)].

6 ADVERSE REACTIONS

The following safety concerns are described elsewhere in the label:

- New or worsening heart failure [see Warnings and Precautions (5.3)]
- Liver Injury [see Warnings and Precautions (5.5)]
- Hypokalemia and hypomagnesemia with potassium-depleting diuretics [see Warnings and Precautions (5.6)]
- QT prolongation [see Warnings and Precautions (5.7)]

6.1 Clinical Trials Experience

The safety evaluation of dronedarone 400 mg twice daily in patients with AF or AFL is based on 5 placebo controlled studies, ATHENA, EURIDIS, ADONIS, ERATO and DAFNE. In these studies, a total of 6285 patients were randomized and treated, 3282 patients with MULTAQ 400 mg twice daily, and 2875 with placebo. The mean exposure across studies was 12 months. In ATHENA, the maximum follow-up was 30 months.

In clinical trials, premature discontinuation because of adverse reactions occurred in 11.8% of the dronedarone-treated patients and in 7.7% of the placebo-treated group. The most common reasons for discontinuation of therapy with MULTAQ were gastrointestinal disorders (3.2 % versus 1.8% in the placebo group) and QT prolongation (1.5% versus 0.5% in the placebo group).

The most frequent adverse reactions observed with MULTAQ 400 mg twice daily in the 5 studies were diarrhea, nausea, abdominal pain, vomiting, and asthenia.

Table 1 displays adverse reactions more common with dronedarone 400 mg twice daily than with placebo in AF or AFL patients, presented by system organ class and by decreasing order of frequency. Adverse laboratory and ECG effects are presented separately in Table 2.

Table 1: Adverse Drug Reactions that Occurred in at Least 1% of Patients and Were More Frequent than Placebo
 | Placebo | Dronedarone 400 mg twice daily
 | (N=2875) | (N=3282)
Gastrointestinal
Diarrhea | 6% | 9%
Nausea | 3% | 5%
Abdominal pain | 3% | 4%
Vomiting | 1% | 2%
Dyspeptic signs and symptoms | 1% | 2%
General
Asthenic conditions | 5% | 7%
Cardiac
Bradycardia | 1% | 3%
Skin and subcutaneous tissue
Including rashes (generalized, macular, maculo-papular, erythematous), pruritus, eczema, dermatitis, dermatitis allergic | 3% | 5%

Photosensitivity reaction and dysgeusia have also been reported at an incidence less than 1% in patients treated with MULTAQ.

The following laboratory data/ECG parameters were reported with MULTAQ 400 mg twice daily.

Table 2: Laboratory data/ECG parameters not necessarily reported as adverse events
 | Placebo | MULTAQ 400 mg twice daily
 | (N=2875) | (N=3282)
Early increases in creatinine ≥10% | 21% | 51%
 | (N=2237) | (N=2701)
QTc prolonged | 19% | 28%

Assessment of demographic factors such as gender or age on the incidence of treatment-emergent adverse events did not suggest an excess of adverse events in any particular sub-group.

6.2 Postmarketing Experience

The following adverse reactions have been identified during post-approval use of MULTAQ. Because these reactions are reported voluntarily from a population of an unknown size, it is not always possible to reliably estimate their frequency or establish a causal relationship to drug exposure.

Cardiac: New or worsening heart failure [see Warnings and Precautions (5.3)]

Hepatic: Liver Injury [see Warnings and Precautions (5.5)]

Respiratory: Postmarketing cases of interstitial lung disease including pneumonitis and pulmonary fibrosis have been reported.

7 DRUG INTERACTIONS

Dronedarone is metabolized primarily by CYP 3A and is a moderate inhibitor of CYP 3A and CYP 2D6 [see Clinical Pharmacology (12.3)]. Dronedarone's blood levels can therefore be affected by inhibitors and inducers of CYP 3A, and dronedarone can interact with drugs that are substrates of CYP 3A and CYP 2D6.

Dronedarone has no significant potential to inhibit CYP 1A2, CYP 2C9, CYP 2C19, CYP 2C8 and CYP 2B6. It has the potential to inhibit P-glycoprotein (P-gP) transport.

Pharmacodynamic interactions can be expected with beta-blockers; calcium antagonists and digoxin [see Drug Interactions (7.1)].

In clinical trials, patients treated with dronedarone received concomitant medications including beta-blockers, digoxin, calcium antagonists (including those with heart rate-lowering effects), statins and oral anticoagulants.

7.1 Pharmacodynamic Interactions

Drugs prolonging the QT interval (inducing Torsade de Pointes)

Co-administration of drugs prolonging the QT interval (such as certain phenothiazines, tricyclic antidepressants, certain macrolide antibiotics, and Class I and III antiarrhythmics) is contraindicated because of the potential risk of Torsade de Pointes-type ventricular tachycardia [see Contraindications (4)].

Digoxin

Digoxin can potentiate the electrophysiologic effects of dronedarone (such as decreased AV-node conduction). In clinical trials, increased levels of digoxin were observed when dronedarone was co-administered with digoxin. Gastrointestinal disorders were also increased.

Because of the pharmacokinetic interaction [see Drug Interaction (7.3)] and possible pharmacodynamic interaction, consider the need for continued digoxin therapy. If digoxin treatment is continued, halve the dose of digoxin, monitor serum levels closely, and observe for toxicity.

Calcium channel blockers

Calcium channel blockers with depressant effects on the sinus and AV nodes could potentiate dronedarone's effects on conduction.

Give low doses of calcium channel blockers initially and increase only after ECG verification of good tolerability [see Drug Interactions (7.3)].

Beta-blockers

In clinical trials, bradycardia was more frequently observed when dronedarone was given in combination with beta-blockers.

Give low dose of beta-blockers initially, and increase only after ECG verification of good tolerability [see Drug Interactions (7.3)].

7.2 Effects of Other Drugs on Dronedarone

Ketoconazole and other potent CYP 3A inhibitors

Repeated doses of ketoconazole, a strong CYP 3A inhibitor, resulted in a 17-fold increase in dronedarone exposure and a 9-fold increase in Cmax. Concomitant use of ketoconazole as well as other potent CYP 3A inhibitors such as itraconazole, voriconazole, ritonavir, clarithromycin, and nefazodone is contraindicated [see Contraindications (4)].

Grapefruit juice

Grapefruit juice, a moderate inhibitor of CYP 3A, resulted in a 3-fold increase in dronedarone exposure and a 2.5-fold increase in Cmax. Therefore, patients should avoid grapefruit juice beverages while taking MULTAQ.

Rifampin and other CYP 3A inducers

Rifampin decreased dronedarone exposure by 80%. Avoid rifampin or other CYP 3A inducers such as phenobarbital, carbamazepine, phenytoin, and St John's wort with dronedarone because they decrease its exposure significantly.

Calcium channel blockers

Verapamil and diltiazem are moderate CYP 3A inhibitors and increase dronedarone exposure by approximately 1.4-to 1.7-fold [see Drug Interactions (7.1, 7.3)].

Pantoprazole

Pantoprazole, a drug that increases gastric pH, did not have a significant effect on dronedarone pharmacokinetics.

7.3 Effects of Dronedarone on Other Drugs

Statins

Dronedarone increased simvastatin/simvastatin acid exposure by 4- and 2-fold, respectively. Because of multiple mechanisms of interaction with statins (CYPs and transporters), follow statin label recommendations for use with CYP 3A and P-gP inhibitors such as dronedarone.

Calcium channel blockers

Dronedarone increases calcium channel blocker (verapamil, diltiazem or nifedipine) exposure by 1.4- to 1.5-fold [see Drug Interactions (7.1)].

Sirolimus, tacrolimus, and other CYP3A substrates with narrow therapeutic range

Dronedarone can increase plasma concentrations of tacrolimus, sirolimus, and other CYP 3A substrates with a narrow therapeutic range when given orally. Monitor plasma concentrations and adjust dosage appropriately.

Beta-blockers and other CYP 2D6 substrates

Dronedarone increased propranolol exposure by approximately 1.3-fold following single dose administration. Dronedarone increased metoprolol exposure by 1.6-fold following multiple dose administration [see Drug Interaction (7.1)]. Other CYP 2D6 substrates, including other beta-blockers, tricyclic antidepressants, and selective serotonin reuptake inhibitors (SSRIs) may have increased exposure upon co-administration with dronedarone.

P-glycoprotein substrates

Digoxin

Dronedarone increased digoxin exposure by 2.5-fold by inhibiting the P-gP transporter [see Drug Interactions (7.1)].

Dabigatran

Exposure to dabigatran is higher when it is administered with dronedarone than when it is administered alone (1.7- to 2-fold).

Other P-gP substrates are expected to have increased exposure when co-administered with dronedarone.

Warfarin and losartan (CYP 2C9 substrates)

Losartan

No interaction was observed between dronedarone and losartan.

Warfarin

When healthy subjects were administered dronedarone 600 mg twice daily, exposure to S-warfarin was higher than when warfarin was administered alone (1.2-fold). Exposure to R-warfarin was unchanged and there were no clinically significant increases in INR.

More patients experienced clinically significant INR elevations (≥ 5) usually within 1 week after starting dronedarone vs. placebo in patients taking oral anticoagulants in ATHENA. However, no excess risk of bleeding was observed in the dronedarone group.

Postmarketing cases of increased INR with or without bleeding events have been reported in warfarin-treated patients initiated on dronedarone. Monitor INR after initiating dronedarone in patients taking warfarin.

Theophylline (CYP 1A2 substrate)

Dronedarone does not increase steady state theophylline exposure.

Oral contraceptives

No decreases in ethinylestradiol and levonorgestrel concentrations were observed in healthy subjects receiving dronedarone concomitantly with oral contraceptives.

8 USE IN SPECIFIC POPULATIONS

8.1 Pregnancy

TERATOGENIC EFFECTS

Pregnancy Category X [see Contraindications (4)]

MULTAQ may cause fetal harm when administered to a pregnant woman. In animal studies, dronedarone was teratogenic in rats at the maximum recommended human dose (MRHD), and in rabbits at half the MRHD. If this drug is used during pregnancy or if the patient becomes pregnant while taking this drug, the patient should be apprised of the potential hazard to the fetus.

When pregnant rats received dronedarone at oral doses greater than or equal to the MRHD (on a mg/m^2 basis), fetuses had increased rates of external, visceral and skeletal malformations (cranioschisis, cleft palate, incomplete evagination of pineal body, brachygnathia, partially fused carotid arteries, truncus arteriosus, abnormal lobation of the liver, partially duplicated inferior vena cava, brachydactyly, ectrodactylia, syndactylia, and anterior and/or posterior club feet). When pregnant rabbits received dronedarone, at a dose approximately half the MRHD (on a mg/m^2 basis), fetuses had an increased rate of skeletal abnormalities (anomalous ribcage and vertebrae, pelvic asymmetry) at doses ≥20 mg/kg (the lowest dose tested and approximately half the MRHD on a mg/m^2 basis).

Actual animal doses: rat (≥80 mg/kg/day); rabbit (≥20 mg/kg)

8.3 Nursing Mothers

It is not known whether MULTAQ is excreted in human milk. Dronedarone and its metabolites are excreted in rat milk. During a pre- and post-natal study in rats, maternal dronedarone administration was associated with minor reduced body-weight gain in the offspring. Because many drugs are excreted in human milk and because of the potential for serious adverse reactions in nursing infants from MULTAQ, discontinue nursing or discontinue the drug [see Contraindications (4)].

8.4 Pediatric Use

Safety and efficacy in children below the age of 18 years have not been established.

8.5 Geriatric Use

More than 4500 patients with AF or AFL aged 65 years or above were included in the MULTAQ clinical program (of whom more than 2000 patients were 75 years or older). Efficacy and safety were similar in elderly and younger patients.

8.6 Renal Impairment

Patients with renal impairment were included in clinical studies. Because renal excretion of dronedarone is minimal [see Clinical Pharmacology (12.3)], no dosing alteration is needed.

8.7 Hepatic Impairment

Dronedarone is extensively metabolized by the liver. There is little clinical experience with moderate hepatic impairment and none with severe impairment. No dosage adjustment is recommended for moderate hepatic impairment [see Contraindications (4) and Clinical Pharmacology (12.3)].

10 OVERDOSAGE

In the event of overdosage, monitor the patient's cardiac rhythm and blood pressure. Treatment should be supportive and based on symptoms.

It is not known whether dronedarone or its metabolites can be removed by dialysis (hemodialysis, peritoneal dialysis or hemofiltration).

There is no specific antidote available.

11 DESCRIPTION

Dronedarone HCl is a benzofuran derivative with the following chemical name:

N-{2-butyl-3-[4-(3-dibutylaminopropoxy)benzoyl]benzofuran-5-yl} methanesulfonamide, hydrochloride.

Dronedarone HCl is a white fine powder that is practically insoluble in water and freely soluble in methylene chloride and methanol.

Its empirical formula is C31H44N2O5 S, HCl with a relative molecular mass of 593.2. Its structural formula is:

MULTAQ is provided as tablets for oral administration.

Each tablet of MULTAQ contains 400 mg of dronedarone (expressed as base).

The inactive ingredients are:

Core of the tablets- hypromellose, starch, crospovidone, poloxamer 407, lactose monohydrate, colloidal silicon dioxide, magnesium stearate.
Coating / polishing of the tablets- hypromellose, polyethylene glycol 6000, titanium dioxide, carnauba wax.

12 CLINICAL PHARMACOLOGY

12.1 Mechanism of Action

The mechanism of action of dronedarone is unknown. Dronedarone has antiarrhythmic properties belonging to all four Vaughan-Williams classes, but the contribution of each of these activities to the clinical effect is unknown.

12.2 Pharmacodynamics

Electrophysiological effects

Dronedarone exhibits properties of all four Vaughn-Williams antiarrhythmic classes, although it is unclear which of these are important in producing dronedarone's clinical effects. The effect of dronedarone on 12-lead ECG parameters (heart rate, PR, and QTc) was investigated in healthy subjects following repeated oral doses up to 1600 mg once daily or 800 mg twice daily for 14 days and 1600 mg twice daily for 10 days. In the dronedarone 400 mg twice daily group, there was no apparent effect on heart rate; a moderate heart rate lowering effect (about 4 bpm) was noted at 800 mg twice daily. There was a clear dose-dependent effect on PR-interval with an increase of +5 ms at 400 mg twice daily and up to +50 ms at 1600 mg twice daily. There was a moderate dose related effect on the QTc-interval with an increase of +10 ms at 400 mg twice daily and up to +25 ms with 1600 mg twice daily.

DAFNE study

DAFNE was a dose-response study in patients with recurrent AF, evaluating the effect of dronedarone in comparison with placebo in maintaining sinus rhythm. The doses of dronedarone in this study were 400, 600, and 800 mg twice a day. In this small study, doses above 400 mg were not more effective and were less well tolerated.

12.3 Pharmacokinetics

Dronedarone is extensively metabolized and has low systemic bioavailability; its bioavailability is increased by meals. Its elimination half life is 13–19 hours.

Absorption

Because of presystemic first pass metabolism the absolute bioavailability of dronedarone without food is low, about 4%. It increases to approximately 15% when dronedarone is administered with a high fat meal. After oral administration in fed conditions, peak plasma concentrations of dronedarone and the main circulating active metabolite (N-debutyl metabolite) are reached within 3 to 6 hours. After repeated administration of 400 mg twice daily, steady state is reached within 4 to 8 days of treatment and the mean accumulation ratio for dronedarone ranges from 2.6 to 4.5. The steady state Cmax and exposure of the main N-debutyl metabolite is similar to that of the parent compound. The pharmacokinetics of dronedarone and its N-debutyl metabolite both deviate moderately from dose proportionality: a 2-fold increase in dose results in an approximate 2.5- to 3.0- fold increase with respect to Cmax and AUC.

Distribution

The in vitro plasma protein binding of dronedarone and its N-debutyl metabolite is >98 % and not saturable. Both compounds bind mainly to albumin. After intravenous (IV) administration the volume of distribution at steady state is about 1400 L.

Metabolism

Dronedarone is extensively metabolized, mainly by CYP 3A. The initial metabolic pathway includes N-debutylation to form the active N-debutyl metabolite, oxidative deamination to form the inactive propanoic acid metabolite, and direct oxidation. The metabolites undergo further metabolism to yield over 30 uncharacterized metabolites. The N-debutyl metabolite exhibits pharmacodynamic activity but is 1/10 to 1/3 as potent as dronedarone

Excretion/Elimination

In a mass balance study with orally administered dronedarone (^14C-labeled) approximately 6% of the labeled dose was excreted in urine, mainly as metabolites (no unchanged compound excreted in urine), and 84% was excreted in feces, mainly as metabolites. Dronedarone and its N-debutyl active metabolite accounted for less than 15% of the resultant radioactivity in the plasma.

After IV administration the plasma clearance of dronedarone ranges from 130 to 150 L/h. The elimination half-life of dronedarone ranges from 13 to 19 hours.

Special populations

Gender

Dronedarone exposures are on average 30% higher in females than in males.

Race

Pharmacokinetic differences related to race were not formally assessed. However, based on a cross study comparison, following single dose administration (400 mg), Asian males (Japanese) have about a 2-fold higher exposure than Caucasian males. The pharmacokinetics of dronedarone in other races has not been assessed.

Elderly

Of the total number of subjects in clinical studies of dronedarone, 73% were 65 years of age and over and 34% were 75 and over. In patients aged 65 years old and above, dronedarone exposures are 23% higher than in patients less than 65 years old [see Use in Specific Populations (8.5)].

Hepatic impairment

In subjects with moderate hepatic impairment, the mean dronedarone exposure increased by 1.3-fold relative to subjects with normal hepatic function and the mean exposure of the N-debutyl metabolite decreased by about 50%. Pharmacokinetic data were significantly more variable in subjects with moderate hepatic impairment.

The effect of severe hepatic impairment on the pharmacokinetics of dronedarone was not assessed [see Contraindications (4)].

Renal impairment

Consistent with the low renal excretion of dronedarone, no pharmacokinetic difference was observed in subjects with mild or moderate renal impairment compared to subjects with normal renal function [see Use in Specific Populations (8.6)]. No pharmacokinetic difference was observed in patients with mild to severe renal impairment in comparison with patients with normal renal function.

13 NONCLINICAL TOXICOLOGY

13.1 Carcinogenesis, Mutagenesis, Impairment of Fertility

In studies in which dronedarone was administered to rats and mice for up to 2 years at doses of up to 70 mg/kg/day and 300 mg/kg/day, respectively, there was an increased incidence of histiocytic sarcomas in dronedarone-treated male mice (300 mg/kg/day or 5× the maximum recommended human dose based on AUC comparisons), mammary adenocarcinomas in dronedarone-treated female mice (300 mg/kg/day or 8× MRHD based on AUC comparisons) and hemangiomas in dronedarone-treated male rats (70 mg/kg/day or 5× MRHD based on AUC comparisons).

Dronedarone did not demonstrate genotoxic potential in the in vivo mouse micronucleus test, the Ames bacterial mutation assay, the unscheduled DNA synthesis assay, or an in vitro chromosomal aberration assay in human lymphocytes. S-9 processed dronedarone, however, was positive in a V79 transfected Chinese hamster V79 assay.

In fertility studies conducted with female rats, dronedarone given prior to breeding and implantation caused an increase in irregular estrus cycles and cessation of cycling at doses ≥10mg/kg (equivalent to 0.12× the MRHD on a mg/m^2 basis).

Corpora lutea, implantations and live fetuses were decreased at 100 mg/kg (equivalent to 1.2× the MRHD on a mg/m^2 basis). There were no reported effects on mating behavior or fertility of male rats at doses of up to 100 mg/kg/day.

13.3 Developmental Toxicity

Dronedarone was teratogenic in rats given oral doses ≥80 mg/kg/day (a dose equivalent to the maximum recommended human dose [MHRD] on a mg/m^2 basis), with fetuses showing external, visceral and skeletal malformations (cranioschisis, cleft palate, incomplete evagination of pineal body, brachygnathia, partially fused carotid arteries, truncus arteriosus, abnormal lobation of the liver, partially duplicated inferior vena cava, brachydactyly, ectrodactylia, syndactylia, and anterior and/or posterior club feet). In rabbits, dronedarone caused an increase in skeletal abnormalities (anomalous ribcage and vertebrae, pelvic asymmetry) at doses ≥20 mg/kg (the lowest dose tested and approximately half the MRHD on a mg/m^2 basis).

14 CLINICAL STUDIES

14.1 ATHENA

ATHENA was a multicenter, multinational, double blind, and randomized placebo-controlled study of dronedarone in 4628 patients with a recent history of AF/AFL who were in sinus rhythm or who were to be converted to sinus rhythm. The objective of the study was to determine whether dronedarone could delay death from any cause or hospitalization for cardiovascular reasons.

Initially patients were to be ≥70 years old, or <70 years old with at least one risk factor (including hypertension, diabetes, prior cerebrovascular accident, left atrial diameter ≥50 mm or LVEF<0.40). The inclusion criteria were later changed such that patients were to be ≥75 years old, or ≥70 years old with at least one risk factor. Patients had to have both AF/AFL and sinus rhythm documented within the previous 6 months. Patients could have been in AF/AFL or in sinus rhythm at the time of randomization, but patients not in sinus rhythm were expected to be either electrically or chemically converted to normal sinus rhythm after anticoagulation.

Subjects were randomized and treated for up to 30 months (median follow-up: 22 months) with either MULTAQ 400 mg twice daily (2301 patients) or placebo (2327 patients), in addition to conventional therapy for cardiovascular diseases that included beta-blockers (71%), ACE inhibitors or angiotensin II receptor blockers (ARBs)(69%), digoxin (14%), calcium antagonists (14%), statins (39%), oral anticoagulants (60%), aspirin (44%), other chronic antiplatelet therapy (6%) and diuretics (54%).

The primary endpoint of the study was the time to first hospitalization for cardiovascular reasons or death from any cause. Time to death from any cause, time to first hospitalization for cardiovascular reasons, and time to cardiovascular death and time to all causes of death were also explored.

Patients ranged in age from 23 to 97 years; 42% were 75 years old or older. Forty-seven percent (47%) of patients were female and a majority was Caucasian (89%). Approximately seventy percent (71%) of those enrolled had no history of heart failure. The median ejection fraction was 60%. Twenty-nine percent (29%) of patients had heart failure, mostly NYHA class II (17%). The majority had hypertension (86%) and structural heart disease (60%).

Results are shown in Table 3. MULTAQ reduced the combined endpoint of cardiovascular hospitalization or death from any cause by 24.2% when compared to placebo. This difference was entirely attributable to its effect on cardiovascular hospitalization, principally hospitalization related to AF.

Other endpoints, death from any cause and first hospitalization for cardiovascular reasons, are shown in Table 3. Secondary endpoints count all first events of a particular type, whether or not they were preceded by a different type of event.

Table 3: Incidence of Endpoint Events
 | Placebo | MULTAQ 400mg BID
 | (N= 2327) | (N= 2301) | HR | 95% CI | p-Value
Primary endpoint
Cardiovascular hospitalization or death from any cause | 913 (39.2%) | 727 (31.6%) | 0.76 | [0.68 – 0.83] | <0.0001
Components of the endpoint (as first event)
- Cardiovascular hospitalization | 856 (36.8%) | 669 (29.1%)
- Death from any cause | 57 (2.4%) | 58 (2.5%)
Secondary endpoints (any time in study)
- Death from any cause | 135 (5.8%) | 115 (5.0%) | 0.86 | [0.67 – 1.11] | 0.24
- Cardiovascular hospitalization | 856 (36.8%) | 669 (29.1%) | 0.74 | [0.67 – 0.82] | <0.0001
Components of the cardiovascular hospitalization endpoint (as first event)
- AF and other supraventricular rhythm disorders | 456 (19.6%) | 292 (12.7%) | 0.61 | [0.53 – 0.71] | <0.0001
- Other | 400 (17.2%) | 377 (16.4%) | 0.89 | [0.77 – 1.03] | 0.11

The Kaplan-Meier cumulative incidence curves showing the time to first event are displayed in Figure 1. The event curves separated early and continued to diverge over the 30 month follow-up period.

Figure 1: Kaplan-Meier Cumulative Incidence Curves from Randomization to First Cardiovascular Hospitalization or Death from any Cause

Reasons for hospitalization included major bleeding (1% in both groups), syncope (1% in both groups), and ventricular arrhythmia (<1% in both groups).

The reduction in cardiovascular hospitalization or death from any cause was generally consistent in all subgroups based on baseline characteristics or medications (ACE inhibitors or ARBs; beta-blockers, digoxin, statins, calcium channel blockers, diuretics) (see Figure 2).

Figure 2: Relative Risk (MULTAQ versus placebo) Estimates with 95% Confidence Intervals According to Selected Baseline Characteristics: First Cardiovascular Hospitalization or Death from any Cause.

a Determined from Cox regression model
b P-value of interaction between baseline characteristics and treatment based on Cox regression model
c Calcium antagonists with heart rate lowering effects restricted to diltiazem, verapamil and bepridil

14.2 EURIDIS and ADONIS

In EURIDIS and ADONIS, a total of 1237 patients in sinus rhythm with a prior episode of AF or AFL were randomized in an outpatient setting and treated with either MULTAQ 400 mg twice daily (n=828) or placebo (n=409) on top of conventional therapies (including oral anticoagulants, beta-blockers, ACE inhibitors or ARBs, chronic antiplatelet agents, diuretics, statins, digoxin, and calcium channel blockers). Patients had at least one ECG-documented AF/AFL episode during the 3 months prior to study entry but were in sinus rhythm for at least one hour. Patients ranged in age from 20 to 88 years, with the majority being Caucasian (97%), male (70%) patients. The most common co-morbidities were hypertension (56.8%) and structural heart disease (41.5%), including coronary heart disease (21.8%). Patients were followed for 12 months.

In the pooled data from EURIDIS and ADONIS as well as in the individual trials, dronedarone delayed the time to first recurrence of AF/AFL (primary endpoint), lowering the risk of first AF/AFL recurrence during the 12-month study period by about 25%,with an absolute difference in recurrence rate of about 11% at 12 months.

14.3 ANDROMEDA

Patients recently hospitalized with symptomatic heart failure and severe left ventricular systolic dysfunction (wall motion index ≤1.2) were randomized to either MULTAQ 400 mg twice daily or matching placebo, with a primary composite end point of all-cause mortality or hospitalization for heart failure. Patients enrolled in ANDROMEDA were predominantly NYHA Class II (40%) and III (57%), and only 25% had AF at randomization. After enrollment of 627 patients and a median follow-up of 63 days, the trial was terminated because of excess mortality in the dronedarone group. Twenty-five (25) patients in the dronedarone group died versus 12 patients in the placebo group (hazard ratio 2.13; 95% CI: 1.07 to 4.25). The main reason for death was worsening heart failure. There were also excess hospitalizations for cardiovascular reasons in the dronedarone group (71 versus 51 for placebo) [see Boxed Warning and Contraindications (4)].

14.4 PALLAS

Patients with permanent AF (AF documented in 2 weeks prior to randomization and at least 6 months prior to randomization in whom cardioversion had failed or was not planned) and additional risk factors for thromboembolism (coronary artery disease, prior stroke or TIA, symptomatic heart failure, LVEF <40%, peripheral arterial occlusive disease, or age >75 with hypertension and diabetes) were randomized to dronedarone 400 mg twice daily or placebo.

After enrollment of 3236 patients (placebo=1617 and dronedarone=1619) and a median follow up of 3.7 months days for placebo and 3.9 for dronedarone, the study was terminated because of a significant increase in

- Mortality: 25 dronedarone vs. 13 placebo (HR, 1.94; CI, 0.99 to 3.79). The majority of deaths in the dronedarone group were classified as arrhythmic/sudden deaths (HR, 3.26; CI: 1.06 to 10.0). Baseline digoxin therapy was reported in 11/13 dronedarone patients who died of arrhythmia. None of the arrhythmic deaths on placebo (4) reported use of digoxin.
- Stroke: 23 dronedarone vs. 10 placebo (HR, 2.32; CI: 1.11 to 4.88). The increased risk of stroke observed with dronedarone was observed in the first two weeks of therapy (10 dronedarone vs. 1 placebo), most of the subjects treated with dronedarone did not have an INR of 2.0 to 3.0.[see Warning and Precaution (5.3)]
- Hospitalizations for heart failure in the dronedarone group: 43 dronedarone vs. 24 placebo (HR, 1.81; CI: 1.10 to 2.99).

16 HOW SUPPLIED/STORAGE AND HANDLING

MULTAQ 400-mg tablets are provided as white film-coated tablets for oral administration, oblong-shaped, engraved with a double wave marking on one side and "4142" code on the other side in:

Bottles of 60 tablets, NDC 54868-3086-0

STORAGE AND HANDLING

Store at 25°C (77°F): excursions permitted to 15–30°C (59–86°F), [see USP controlled room temperature].

17 PATIENT COUNSELING INFORMATION

17.1 Information for Patients

[See Medication Guide (17.2)]

MULTAQ should be administered with a meal. Warn patients not to take MULTAQ with grapefruit juice.

If a dose is missed, patients should take the next dose at the regularly scheduled time and should not double the dose.

Advise patients to consult a physician if they develop signs or symptoms of heart failure such as acute weight gain, dependent edema, or increasing shortness of breath.

Advise patients to immediately report any symptoms of potential liver injury (such as anorexia, nausea, vomiting, fever, malaise, fatigue, right upper quadrant abdominal discomfort, jaundice, dark urine or itching) to their physician.

Advise patients to inform their physician of any history of heart failure, rhythm disturbance other than atrial fibrillation or flutter or predisposing conditions such as uncorrected hypokalemia.

MULTAQ may interact with some drugs; therefore, advise patients to report to their doctor the use of any other prescription, non-prescription medication or herbal products, particularly St. John's wort.

Medication Guide
MULTAQ (MUL-tak)
(dronedarone) Tablets

Read this Medication Guide before you start taking MULTAQ and each time you get a refill. There may be new information. This information does not take the place of talking with your doctor about your medical condition or your treatment.

What is the most important information I should know about MULTAQ?

1. MULTAQ is not for people with heart failure with symptoms which recently worsened or for people with severe heart failure. People with these conditions who take MULTAQ have an increased chance of dying. Heart failure means your heart does not pump blood through your body as well as it should.

Do not take MULTAQ if you have symptoms of heart failure which recently worsened or if you have severe heart failure.

Call your doctor right away if you have any signs and symptoms of heart failure:

- shortness of breath or wheezing at rest
- wheezing, chest tightness or coughing up frothy sputum at rest, nighttime or after minor exercise
- trouble sleeping or waking up at night because of breathing problems
- using more pillows to prop yourself up at night so you can breathe more easily
- gaining more than 5 pounds quickly
- increasing swelling of feet or legs

2. MULTAQ is not for people with a type of atrial fibrillation (irregular heart rhythm) called permanent atrial fibrillation (AF). In permanent AF, your heartbeat stays in atrial fibrillation and will not or cannot be changed back to a normal rhythm. Your doctor will monitor your heart rhythm regularly to make sure your heartbeat keeps a normal rhythm.

Do not take MULTAQ if you have permanent AF.

Call your doctor right away if you notice that your pulse is irregular. This is a sign that you are in atrial fibrillation.

3. MULTAQ may cause liver problems, including life-threatening liver failure. Your doctor may order blood tests to check your liver before you start taking MULTAQ and during treatment. In some cases MULTAQ treatment may need to be stopped. Tell your doctor right away if you develop any of these signs and symptoms of liver problems:
  - loss of appetite, nausea, vomiting
  - fever, feeling unwell, unusual tiredness
  - itching
  - yellowing of the skin or the whites of the eyes (jaundice)
  - unusual darkening of the urine
  - right upper stomach area pain or discomfort

What is MULTAQ?

MULTAQ is a prescription medicine used to lower the chance that you would need to go into the hospital for atrial fibrillation. It is meant for people who have had atrial fibrillation in the past but are now in normal rhythm.

It is not known if MULTAQ is safe and effective in children younger than age 18 years old.

Who should not take MULTAQ?

See "What is the most important information I should know about taking MULTAQ?"

Do not take MULTAQ if:

- You are in atrial fibrillation and your doctor is not planning to change you back into normal rhythm
- You have symptoms of heart failure which recently worsened or you have severe heart failure
- You have severe liver problems or had liver problems after using amiodarone (a medicine for abnormal heart rhythm)
- You take certain medicines that can change the amount of MULTAQ that gets into your body. Do not use these medicines with MULTAQ:
  - Nefazodone for depression
  - Norvir® (ritonavir) for HIV infection
  - Nizoral® (ketoconazole), and Sporanox® (itraconazole), and Vfend® (voriconazole) for fungal infections
  - Ketek® (telithromycin), Biaxin® (clarithromycin) for bacterial infections
  - Cyclosporine for organ transplant
- You take certain medicines that can lead to a dangerous abnormal heart rhythm:
  - Some medicines for mental illness called phenothiazines
  - Some medicines for depression called tricyclic antidepressants
  - Some medicines for abnormal heart rhythm or fast heartbeat
  - Some medicines for bacterial infection
  Ask your doctor if you are not sure if your medicine is one that is listed above.
- You are pregnant or plan to become pregnant. It is not known if MULTAQ will harm your unborn baby. Talk to your doctor if you are pregnant or plan to become pregnant.
  - Women who may become pregnant should use effective birth control (contraception) while taking MULTAQ. Talk to your doctor about the best birth control methods for you.
- You are breast-feeding or plan to breastfeed. It is not known if MULTAQ passes into your breast milk. You and your doctor should decide if you will take MULTAQ or breastfeed. You should not do both.

What should I tell my doctor before starting MULTAQ?

- If you have any other heart problems
- Tell your doctor about all the medicines you take, including any new medicines. Include all prescription and non-prescription medicines, vitamins and herbal remedies. MULTAQ and certain other medicines can react with each other, causing serious side effects. Know the medicines you take. Keep a list of them and show it to your doctor and pharmacist when you get a new medicine.

Be sure to tell your doctor and pharmacist if you take:

- medicine for high blood pressure, chest pain, or other heart conditions
- statin medicine to lower blood cholesterol
- medicine for TB (tuberculosis)
- medicine for seizures
- medicine for organ transplant
- herbal supplement called St. John's wort

Some of these medicines could keep MULTAQ from working well or make it more likely for you to have side effects.

How should I take MULTAQ?

- Take MULTAQ exactly as your doctor tells you.
- Take MULTAQ two times a day with food, once with your morning meal and once with your evening meal.
- Do not stop taking MULTAQ even if you are feeling well for a long time. The medicine may be working.
- If you miss a dose, wait and take your next dose at your regular time. Do not take 2 doses at the same time. Do not try to make up for a missed dose.

What should I avoid while taking MULTAQ?

Do not drink grapefruit juice while you take MULTAQ. Grapefruit juice can increase the amount of MULTAQ in your blood and increase the likelihood that you will have a side effect of MULTAQ.

What are the possible side effects of MULTAQ?

MULTAQ may cause serious side effects, including:

- See "What is the most important information I should know about MULTAQ?"
- Slowed heartbeat (bradycardia)

The most common side effects of MULTAQ include:

- Stomach problems such as
  - diarrhea
  - nausea
  - vomiting
  - stomach area (abdominal) pain
  - indigestion
- feeling tired and weak
- skin problems such as redness, rash, and itching

Tell your doctor about any side effect that bothers you or that does not go away. These are not all the possible side effects of MULTAQ. For more information ask your doctor or pharmacist.

Call your doctor for medical advice about side effects. You may report side effects to FDA at 1-800-FDA-1088.

How should I store MULTAQ?

Store MULTAQ at room temperature (59–86°F or 15–30°C).

Keep MULTAQ and all medicines out of the reach of children.

General information about MULTAQ

Medicines are sometimes used for purposes not mentioned in a Medication Guide. Do not use MULTAQ for a condition for which it was not prescribed. Do not give MULTAQ to other people, even if they have the same symptoms or condition. It may harm them.

This Medication Guide summarizes the most important information about MULTAQ. If you would like more information:

- Talk with your doctor
- Ask your doctor or pharmacist for information about MULTAQ that was written for health-care professionals
- For the latest information and Medication Guide, visit www.sanofi-aventis.us or call sanofi-aventis Medical Information Services at 1-800-633-1610 option 1. The Medication Guide may have changed since this copy was printed.

What are the ingredients in MULTAQ?

Active ingredient: dronedarone

Inactive ingredients: hypromellose, starch, crospovidone, poloxamer 407, lactose monohydrate, colloidal silicon dioxide, magnesium stearate polyethylene glycol 6000, titanium dioxide, carnauba wax

This Medication Guide has been approved by the U.S. Food and Drug Administration.
Issued December 2011

Manufactured by Sanofi Winthrop Industrie
1, rue de la Vierge
33440 Ambares, France

©sanofi-aventis, 2011
All rights reserved.

MULTAQ is a trademark of sanofi-aventis.

The brands listed are the registered trademarks of their respective owners and are not trademarks of sanofi-aventis U.S. LLC.

sanofi-aventis U.S. LLC
Bridgewater, NJ 08807

Additional bar code label applied by:
Physicians Total Care, Inc.
Tulsa, Oklahoma 74146

PACKAGE LABEL

PRINCIPAL DISPLAY PANEL - 60 Tablet Bottle

Rx ONLY

MULTAQ®
(dronedarone)
Tablets 400mg

Dispense with Medication Guide.

60 Tablets